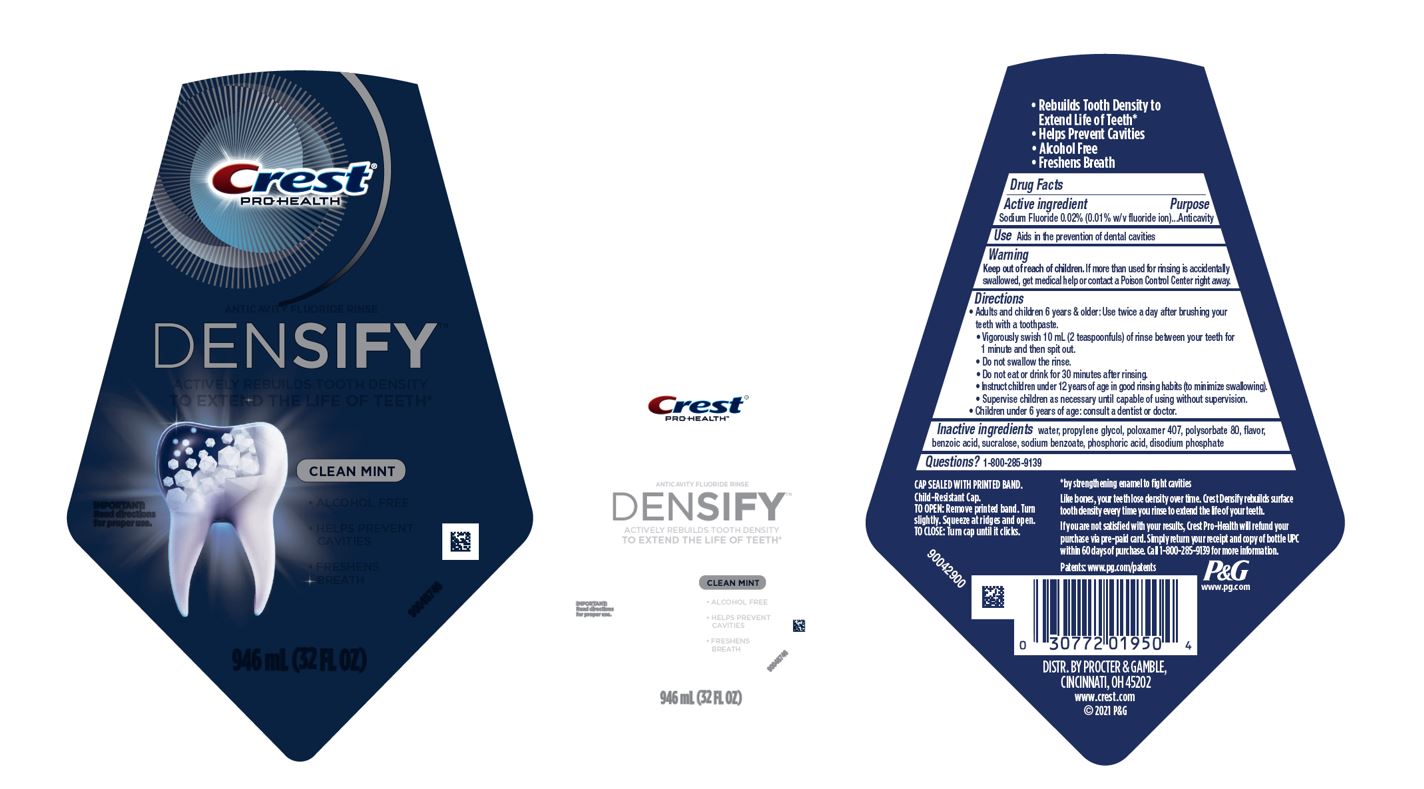 DRUG LABEL: Crest Pro Health
NDC: 69423-882 | Form: RINSE
Manufacturer: The Procter & Gamble Manufacturing Company
Category: otc | Type: HUMAN OTC DRUG LABEL
Date: 20250731

ACTIVE INGREDIENTS: SODIUM FLUORIDE 0.1 mg/1 mL
INACTIVE INGREDIENTS: BENZOIC ACID; WATER; PHOSPHORIC ACID; SODIUM BENZOATE; POLYSORBATE 80; POLOXAMER 407; SUCRALOSE; SODIUM PHOSPHATE, DIBASIC, ANHYDROUS; PROPYLENE GLYCOL

Crest Pro Health Densify Rinse

Drug Facts

Active ingredient

Sodium Fluoride 0.02% (0.01% w/v fluoride ion)

Purpose

Anticavity

Use

Aids in the prevention of dental cavities

Warning

Keep out of reach of children. If more than used for rinsing is accidentally swallowed, get medical help or contact a Poison Control Center right away.

Directions

- Adults and children 6 years & older:
  - Use twice a day after brushing your teeth with a toothpaste.
  - Vigorously swish 10 mL (2 teaspoonfuls) of rinse between your teeth for 1 minute and then spit out.
  - Do not swallow the rinse.
  - Do not eat or drink for 30 minutes after rinsing.
  - Instruct children under 12 years of age in good rinsing habits (to minimize swallowing).
  - Supervise children as necessary until capable of using without supervision.
- Children under 6 years of age: consult a dentist or doctor.

Inactive ingredients

water, propylene glycol, poloxamer 407, polysorbate 80, flavor, benzoic acid, sucralose, sodium benzoate, phosphoric acid, disodium phosphate

Questions?

1-800-285-9139

DISTR. BY PROCTER & GAMBLE,

CINCINNATI, OH 45202

PRINCIPAL DISPLAY PANEL - 946 mL Bottle Label

Crest®

PRO HEALTH™

ANTICAVITY FLUORIDE RINSE

DENSIFY™

ACTIVELY REBUILDS TOOTH DENSITY

TO EXTEND THE LIFE OF TEETH*

CLEAN MINT

• ALCOHOL FREE

• HELPS PREVENT CAVITIES

• FRESHENS BREATH

IMPORTANT: Read directions for proper use.

946 mL (32 FL OZ)